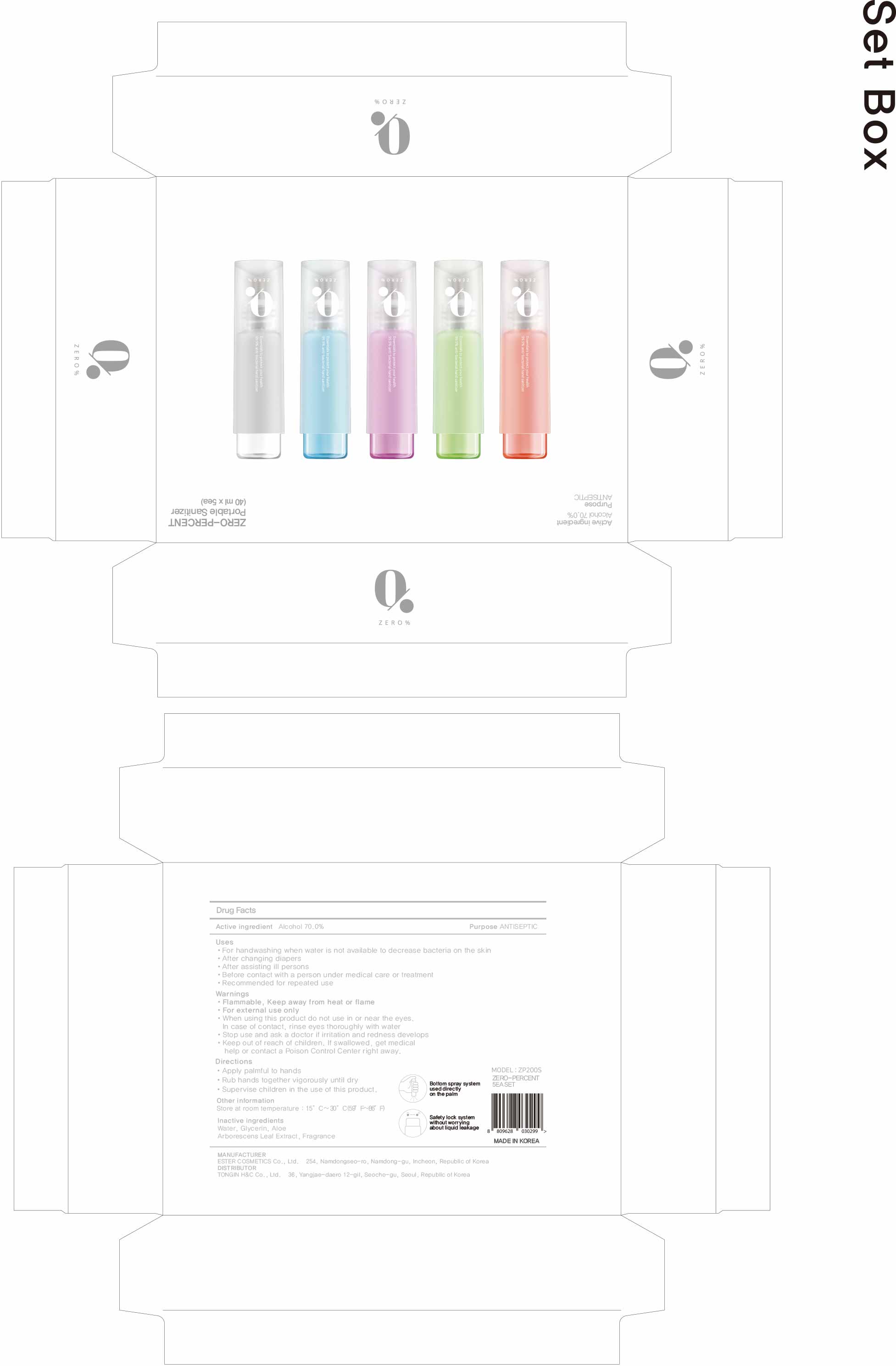 DRUG LABEL: ZERO-PERCENT Portable Sanitizer
NDC: 74004-047 | Form: KIT | Route: TOPICAL
Manufacturer: Ester Co., Ltd.
Category: otc | Type: HUMAN OTC DRUG LABEL
Date: 20201006

ACTIVE INGREDIENTS: ALCOHOL 28 mL/40 mL; ALCOHOL 28 mL/40 mL; ALCOHOL 28 mL/40 mL; ALCOHOL 28 mL/40 mL; ALCOHOL 28 mL/40 mL
INACTIVE INGREDIENTS: GLYCERIN; ALOE ARBORESCENS LEAF; WATER; GLYCERIN; ALOE ARBORESCENS LEAF; WATER; GLYCERIN; ALOE ARBORESCENS LEAF; WATER; GLYCERIN; ALOE ARBORESCENS LEAF; WATER; GLYCERIN; ALOE ARBORESCENS LEAF; WATER

[7] ZERO-PERCENT Portable Sanitizer
Set product
4 fragrance, 1 fragrance-free